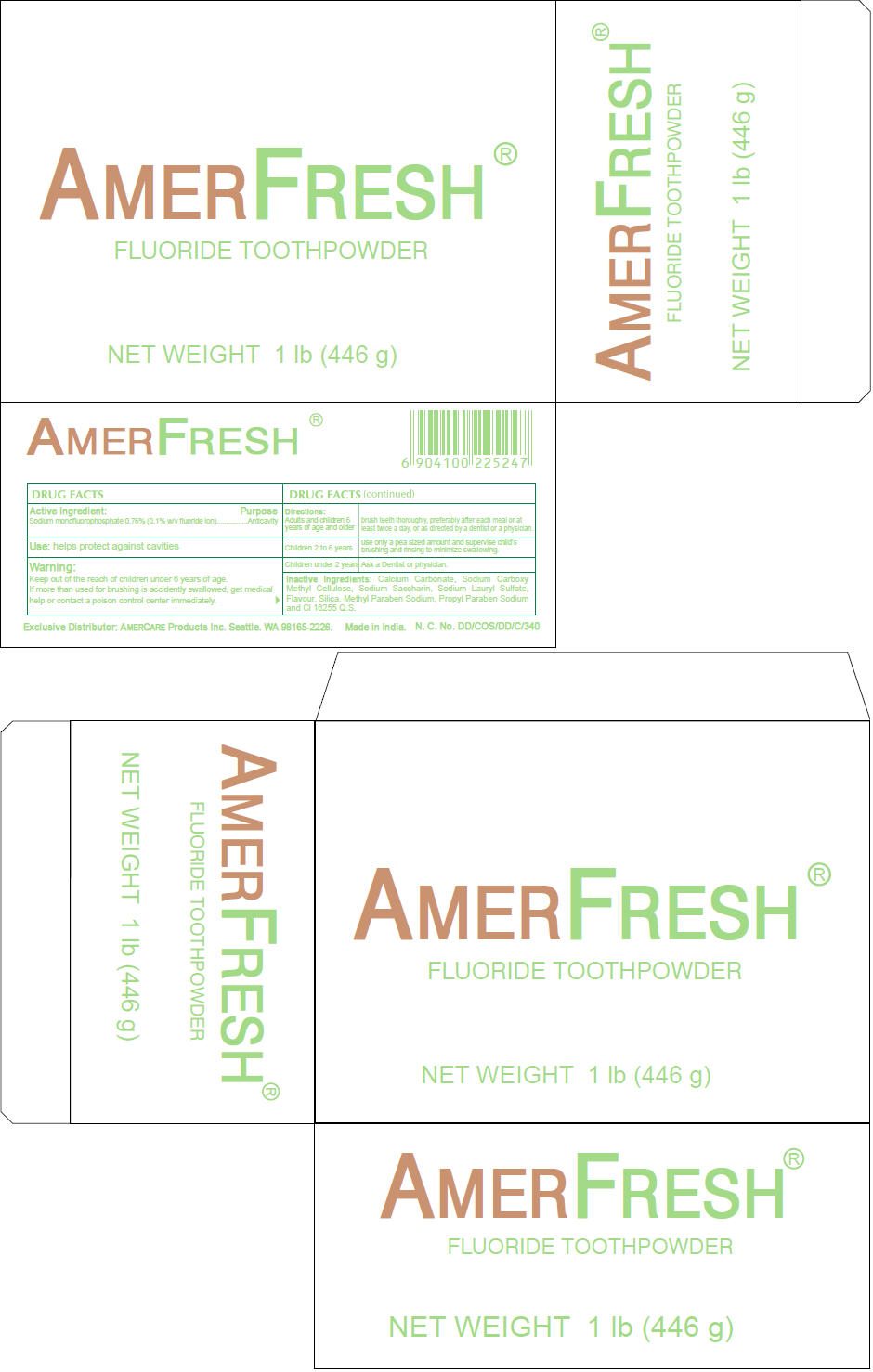 DRUG LABEL: Amerfresh
NDC: 51460-0502 | Form: POWDER
Manufacturer: Amercare Products Inc
Category: otc | Type: HUMAN OTC DRUG LABEL
Date: 20110512

ACTIVE INGREDIENTS: Sodium Monofluorophosphate 0.76 g/100 g
INACTIVE INGREDIENTS: Calcium Carbonate 94.98 g/100 g; Carboxymethylcellulose Sodium; Saccharin Sodium; Sodium Lauryl Sulfate; Methylparaben Sodium; Propylparaben Sodium; Silicon Dioxide; Ponceau 4R

AMERFRESH®
FLUORIDE TOOTHPOWDER

DRUG FACTS

Active Ingredient

Sodium monofluorophosphate 0.76% (0.1% w/v fluoride ion)

Purpose

Anticavity

Use

helps protect against cavities

Warning

KEEP OUT OF REACH OF CHILDREN

Keep out of the reach of children under 6 years of age.

If more than used for brushing is accidently swallowed, get medical help or contact a poison control center immediately.

Directions

Adults and children 6 years of age and older | brush teeth thoroughly, preferably after each meal or at least twice a day, or as directed by a dentist or a physician.
Children 2 to 6 years | use only a pea sized amount and supervise child's brushing and rinsing to minimize swallowing.
Children under 2 years | Ask a Dentist or physician.

Inactive Ingredients

Calcium Carbonate, Sodium Carboxy Methyl Cellulose, Sodium Saccharin, Sodium Lauryl Sulfate, Flavour, Silica, Methyl Paraben Sodium, Propyl Paraben Sodium and Cl 16255 Q.S.

Exclusive Distributor: AMERCARE Products Inc. Seattle. WA 98165-2226.

PRINCIPAL DISPLAY PANEL - 446 g Carton

AMERFRESH®
FLUORIDE TOOTHPOWDER

NET WEIGHT 1 lb (446 g)